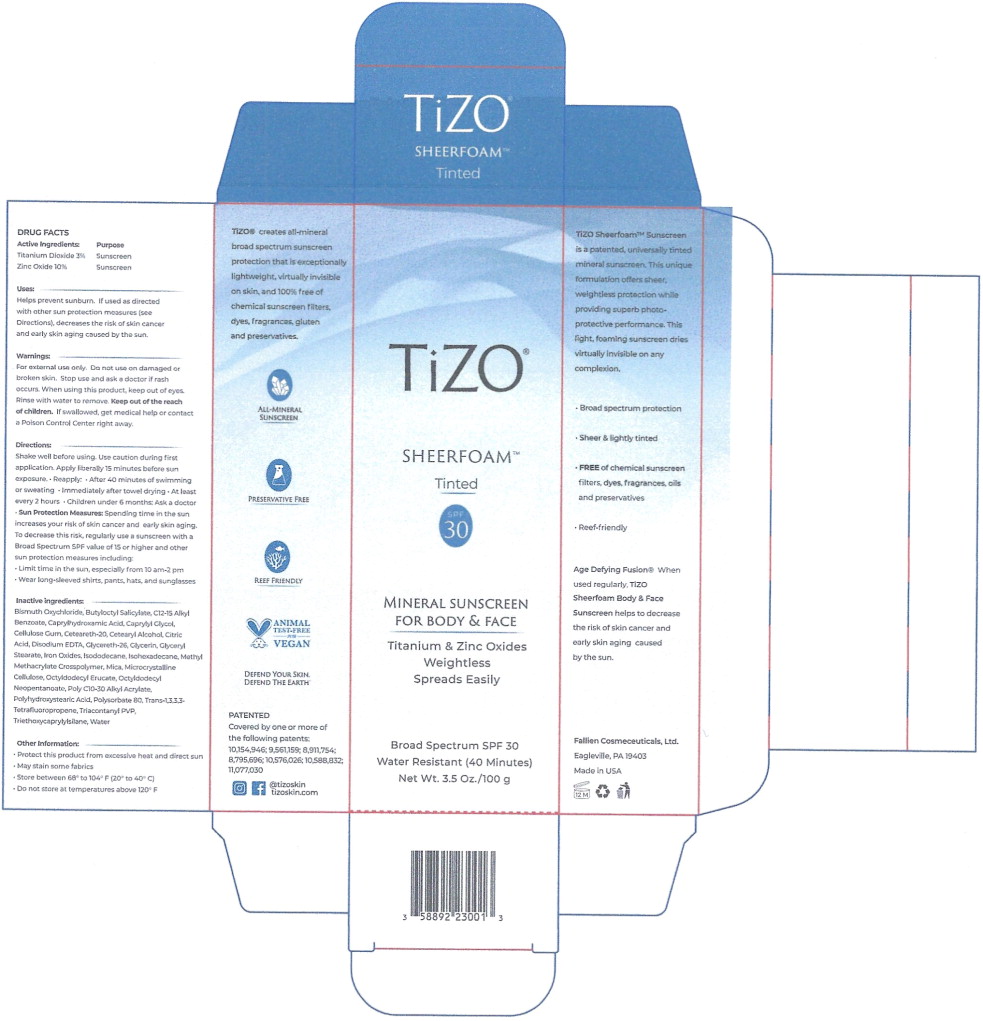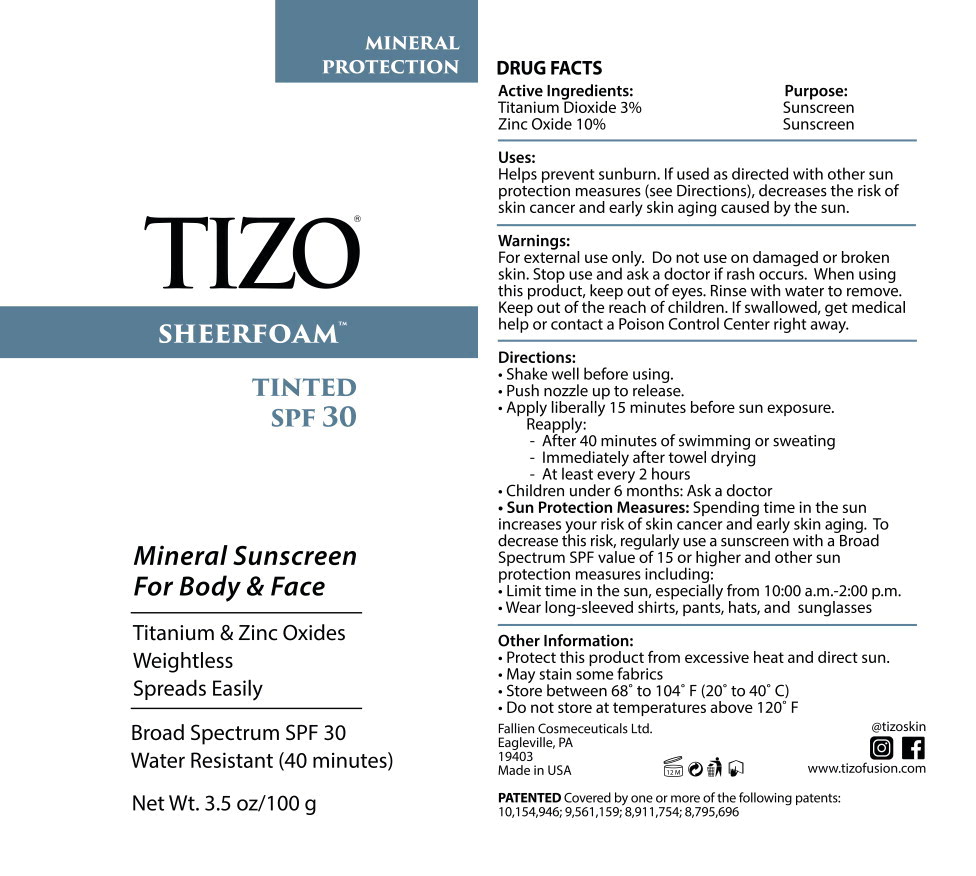 DRUG LABEL: TiZO SheerFoam - Tinted
NDC: 58892-230 | Form: AEROSOL, FOAM
Manufacturer: Fallien Cosmeceuticals, LTD
Category: otc | Type: HUMAN OTC DRUG LABEL
Date: 20241029

ACTIVE INGREDIENTS: TITANIUM DIOXIDE 30 mg/1 g; ZINC OXIDE 100 mg/1 g
INACTIVE INGREDIENTS: BISMUTH OXYCHLORIDE; BUTYLOCTYL SALICYLATE; ALKYL (C12-15) BENZOATE; CAPRYLHYDROXAMIC ACID; CAPRYLYL GLYCOL; CARBOXYMETHYLCELLULOSE SODIUM, UNSPECIFIED FORM; POLYOXYL 20 CETOSTEARYL ETHER; CETOSTEARYL ALCOHOL; CITRIC ACID MONOHYDRATE; EDETATE DISODIUM ANHYDROUS; GLYCERETH-26; GLYCERIN; GLYCERYL MONOSTEARATE; FERRIC OXIDE RED; FERRIC OXIDE YELLOW; FERROSOFERRIC OXIDE; ISODODECANE; METHYL METHACRYLATE/GLYCOL DIMETHACRYLATE CROSSPOLYMER; MICA; MICROCRYSTALLINE CELLULOSE; OCTYLDODECYL ERUCATE; OCTYLDODECYL NEOPENTANOATE; BEHENYL ACRYLATE POLYMER; POLYHYDROXYSTEARIC ACID (2300 MW); POLY(METHYL METHACRYLATE; 450000 MW); POLYSORBATE 80; 1,3,3,3-TETRAFLUOROPROPENE, (1E)-; TRICONTANYL POVIDONE; TRIETHOXYCAPRYLYLSILANE; WATER

Active Ingredients:

Titanium Dioxide 3%

Zinc Oxide 10%

Purpose

Sunscreen

Sunscreen

Uses:

Helps prevent sunburn. If used as directed with other sun protection measures (see Directions), decreases the risk of skin cancer and early skin aging caused by the sun.

Warnings:

For external use only.

Do not use on damaged or broken skin.

Stop use and ask a doctor if rash occurs.

When using this product, keep out of eyes. Rinse with water to remove.

KEEP OUT OF REACH OF CHILDREN

Keep out of the reach of children.If swallowed, get medical help or contact a Poison Control Center right away.

Directions:

Shake well before using. Use caution during first application. Apply liberally 15 minutes before sun exposure.

- Reapply:
  - After 40 minutes of swimming or sweating
  - Immediately after towel drying
  - At least every 2 hours
  - Children under 6 months: Ask a doctor
- Sun Protection Measures: Spending time in the sun increases your risk of skin cancer and early skin aging. To decrease this risk, regularly use a sunscreen with a Broad Spectrum SPF value of 15 or higher and other sun protection measures including:
- Limit time in the sun, especially from 10 am-2 pm
- Wear long-sleeved shirts, pants, hats, and sunglasses

Inactive ingredients:

Bismuth Oxychloride, Butyloctyl Salicylate, C12-15 Alkyl Benzoate, Caprylhydroxamic Acid, Caprylyl Glycol, Cellulose Gum. Ceteareth-20, Cetearyl Alcohol. Citric Acid, Disodium EDTA, Glycereth-26, Glycerin, Glyceryl Stearate, Iron Oxides, Isododecane, Isohexadecane, Methyl Methacrylate Crosspolymer, Mica. Macrocrystalline Cellulose, Octyldodecyl Erucate, Octyldodecyl Neopentanoate, Poly C10-30 Alkyl Acrylate, Polyhydroxystearic Acid. Polysorbate 80, Trans-1,3,3,3- Tetrafluoropropene, Triacontanyl PVP, Triethoxycaprylylsilane, Water

Other Information:

- Protect this product from excessive heat and direct sun
- May stain some fabrics
- Store between 68° to 104° F (20° to 40°C)
- Do not store at temperatures above 120° F

Keep out of the reach of children.

Principal Display Panel – 1 Can Carton Label

TiZO®

SHEERFOAM™

Tinted

SPF
30

MINERAL SUNSCREEN
FOR BODY & FACE

Titanium & Zinc Oxides

Weightless

Spreads Easily

Broad Spectrum SPF 30

Water Resistant (40 minutes)

Net Wt. 3.5 Oz/100 g

Principal Display Panel – 100g Can Label

MINERAL
PROTECTION

TIZO®
SHEERFOAM™

TINTED
SPF 30

Mineral Sunscreen
For Body & Face

Titanium & Zinc Oxides

Weightless

Spreads Easily

Broad Spectrum SPF 30

Water Resistant (40 minutes)

Net Wt. 3.5 oz/100 g